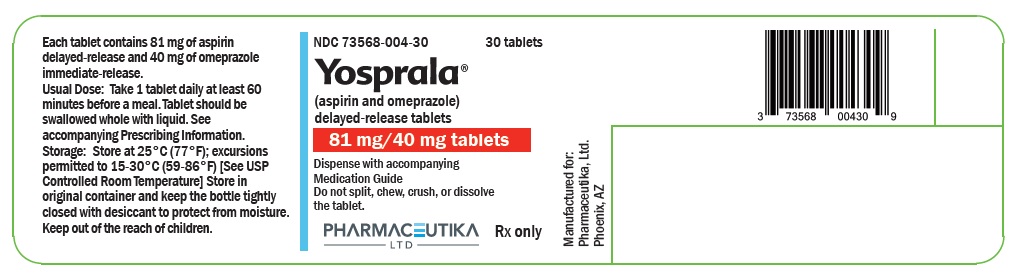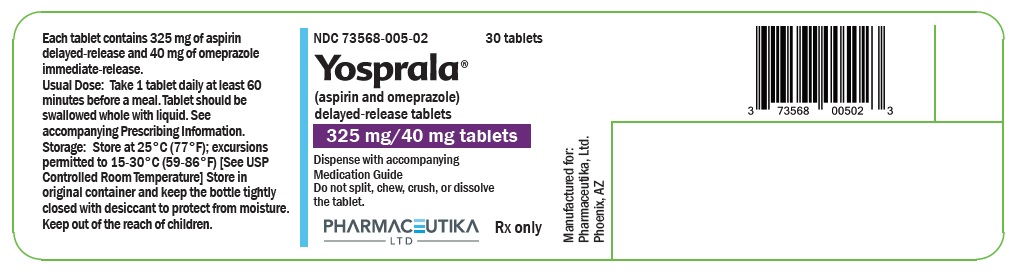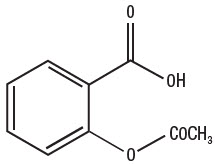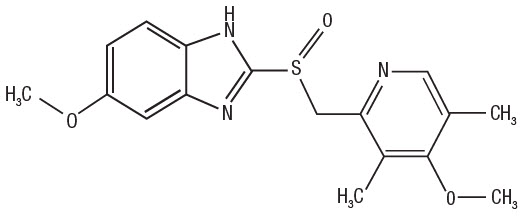 DRUG LABEL: Yosprala
NDC: 73568-004 | Form: TABLET, FILM COATED
Manufacturer: PHARMACEUTIKA LTD
Category: prescription | Type: HUMAN PRESCRIPTION DRUG LABEL
Date: 20200130

ACTIVE INGREDIENTS: aspirin 81 mg/1 1; omeprazole 40 mg/1 1
INACTIVE INGREDIENTS: MICROCRYSTALLINE CELLULOSE; STARCH, CORN; SILICON DIOXIDE; stearic acid; methacrylic acid - ethyl acrylate copolymer (1:1) type A; triethyl citrate; glyceryl monostearate; polysorbate 80; titanium dioxide; HYPROMELLOSE, UNSPECIFIED; POLYETHYLENE GLYCOL, UNSPECIFIED; polydextrose; triacetin; ferric oxide yellow; FD&C blue no. 2; talc; sodium phosphate, dibasic, anhydrous; carnauba wax; POVIDONE, UNSPECIFIED

HIGHLIGHTS OF PRESCRIBING INFORMATION

These highlights do not include all the information needed to use YOSPRALA™ safely and effectively. See full prescribing information for YOSPRALA.
YOSPRALA (aspirin and omeprazole) delayed-release tablets, for oral use
Initial U.S. Approval: 2016

RECENT MAJOR CHANGES

Warnings and Precautions, Fundic Gland Polyps (5.19) | 06/2018

1 INDICATIONS AND USAGE

YOSPRALA is a combination of aspirin, an anti-platelet agent, and omeprazole, a proton pump inhibitor (PPI), indicated for patients who require aspirin for secondary prevention of cardiovascular and cerebrovascular events and who are at risk of developing aspirin associated gastric ulcers.

The aspirin component of YOSPRALA is indicated for:

- reducing the combined risk of death and nonfatal stroke in patients who have had ischemic stroke or transient ischemia of the brain due to fibrin platelet emboli,
- reducing the combined risk of death and nonfatal MI in patients with a previous MI or unstable angina pectoris,
- reducing the combined risk of MI and sudden death in patients with chronic stable angina pectoris,
- use in patients who have undergone revascularization procedures (Coronary Artery Bypass Graft [CABG] or Percutaneous Transluminal Coronary Angioplasty [PTCA]) when there is a pre-existing condition for which aspirin is already indicated.

The omeprazole component of YOSPRALA is indicated for decreasing the risk of developing aspirin associated gastric ulcers in patients at risk for developing aspirin-associated gastric ulcers due to age (≥ 55) or documented history of gastric ulcers. (1)

Limitations of Use:

- Not for use as the initial dose of aspirin therapy during onset of acute coronary syndrome, acute myocardial infarction or before percutaneous coronary intervention. (1)
- Has not been shown to reduce the risk of gastrointestinal bleeding due to aspirin. (1)
- Do not substitute YOSPRALA with the single-ingredient products of aspirin and omeprazole. (1)

2 DOSAGE AND ADMINISTRATION

- Recommended dosage: One tablet daily at least 60 minutes before a meal. (2.1, 2.2)
- Do not split, chew, crush or dissolve the tablet. (2.2)

3 DOSAGE FORMS AND STRENGTHS

Delayed-Release Tablets (3):

- 81 mg delayed-release aspirin/40 mg immediate-release omeprazole
- 325 mg delayed-release aspirin/40 mg immediate-release omeprazole

4 CONTRAINDICATIONS

- History of asthma, urticaria, or other allergic-type reactions after taking aspirin or other NSAIDs. (4)
- In pediatric patients with suspected viral infections, with or without fever, because of the risk of Reye's Syndrome. (4)
- Known hypersensitivity to aspirin, omeprazole, substituted benzimidazoles or to any of the excipients of YOSPRALA. (4)
- Patients receiving rilpivirine-containing products. (4, 7)

5 WARNINGS AND PRECAUTIONS

- Coagulation Abnormalities: Risk of increased bleeding time with aspirin, especially in patients with inherited (hemophilia) or acquired (liver disease or vitamin K deficiency) bleeding disorders. Monitor patients for signs of increased bleeding. (5.1)
- GI Adverse Reactions (including ulceration and bleeding): Monitor for signs and symptoms and discontinue treatment if bleeding occurs. (5.2)
- Bleeding Risk with Use of Alcohol: Avoid heavy alcohol use (three or more drinks every day). (5.3)
- Reduction in Antiplatelet Activity with Clopidogrel due to Interference with CYP2C19 Metabolism: Consider other antiplatelet therapy. (5.4, 7)
- Reduction in Efficacy of Ticagrelor: Avoid use with the 325/40 strength of YOSPRALA. (5.5, 7)
- Renal Failure: Avoid YOSPRALA in patients with severe renal failure. (5.6, 8.6)
- Gastric Malignancy: In adults, response to gastric symptoms does not preclude the presence of gastric malignancy; Consider additional follow-up and diagnostic testing. (5.7)
- Acute Interstitial Nephritis: Observed in patients taking PPIs. (5.8)
- Clostridium difficile-Associated Diarrhea: PPI therapy may be associated with increased risk; use lowest dose and shortest duration of treatment. (5.9)
- Bone Fracture: Long-term and multiple daily dose PPI therapy may be associated with an increased risk for osteoporosis-related fractures of the hip, wrist or spine; use lowest dose and shortest duration of treatment. (5.10)
- Cutaneous and Systemic Lupus Erythematosus: Mostly cutaneous; new onset or exacerbation of existing disease; discontinue YOSPRALA and refer to specialist for evaluation. (5.11)
- Hepatic Impairment: Avoid YOSPRALA in patients with all degrees of hepatic impairment. (5.12, 8.7)
- Cyanocobalamin (Vitamin B-12) Deficiency: Daily long-term use (e.g., longer than 3 years) of PPI may lead to malabsorption or deficiency. (5.13)
- Hypomagnesemia: Reported rarely with prolonged treatment with PPIs; consider monitoring magnesium levels. (5.14)
- Reduced Effect of Omeprazole with St. John's Wort or Rifampin: Avoid concomitant use. (5.15, 7)
- Interactions with Diagnostic Investigations for Neuroendocrine Tumors: Increased Chromogranin A (CgA) levels may interfere with diagnostic investigations for neuroendocrine tumors; temporarily stop YOSPRALA at least 14 days before assessing CgA levels (5.16, 7)
- Bone Marrow Toxicity with Methotrexate, especially in the elderly or renally impaired: Use with PPIs may elevate and/or prolong serum levels of methotrexate and/or its metabolite, possibly leading to toxicity. With high dose methotrexate, consider a temporary withdrawal of YOSPRALA. (5.17, 7)
- Premature closure of the ductus arteriosus: Avoid use in pregnant women starting at 30 weeks gestation. (5.18, 8.1)
- Abnormal Laboratory Tests: Aspirin has been associated with elevated hepatic enzymes, blood urea nitrogen and serum creatinine, hyperkalemia, proteinuria, and prolonged bleeding time. (5.19)
- Fundic Gland Polyps: Risk increases with long-term use, especially beyond one year. Use the shortest duration of therapy. (5.20)

7 DRUG INTERACTIONS

See full prescribing information for a list of clinically important drug interactions. (7)

8 USE IN SPECIFIC POPULATIONS

- Lactation: Breastfeeding not recommended. (8.2)
- Females and Males of Reproductive Potential Infertility: NSAIDs are associated with reversible infertility. Consider withdrawal of YOSPRALA in women who have difficulties conceiving. (8.3)

FULL PRESCRIBING INFORMATION

1 INDICATIONS AND USAGE

YOSPRALA, a combination of aspirin and omeprazole, is indicated for patients who require aspirin for secondary prevention of cardiovascular and cerebrovascular events and who are at risk of developing aspirin associated gastric ulcers.

The aspirin component of YOSPRALA is indicated for:

- reducing the combined risk of death and nonfatal stroke in patients who have had ischemic stroke or transient ischemia of the brain due to fibrin platelet emboli,
- reducing the combined risk of death and nonfatal MI in patients with a previous MI or unstable angina pectoris,
- reducing the combined risk of MI and sudden death in patients with chronic stable angina pectoris,
- use in patients who have undergone revascularization procedures (Coronary Artery Bypass Graft [CABG] or Percutaneous Transluminal Coronary Angioplasty [PTCA]) when there is a pre-existing condition for which aspirin is already indicated.

The omeprazole component of YOSPRALA is indicated for decreasing the risk of developing aspirin-associated gastric ulcers in patients at risk for developing aspirin-associated gastric ulcers due to age (≥ 55) or documented history of gastric ulcers.

Limitations of Use:

- YOSPRALA contains a delayed-release formulation of aspirin and it is not for use as the initial dose of aspirin therapy during onset of acute coronary syndrome, acute myocardial infarction or before percutaneous coronary intervention (PCI), for which immediate-release aspirin therapy is appropriate.
- YOSPRALA has not been shown to reduce the risk of gastrointestinal bleeding due to aspirin.
- Do not substitute YOSPRALA with the single-ingredient products of aspirin and omeprazole.

2 DOSAGE AND ADMINISTRATION

2.1 Recommended Dosage

- Take one tablet daily.
- YOSPRALA is available in combinations that contain 81 mg or 325 mg of aspirin. Generally 81 mg of aspirin has been accepted as an effective dose for secondary cardiovascular prevention. Providers should consider the need for 325 mg and refer to current clinical practice guidelines.

2.2 Administration Instructions

- Take YOSPRALA once daily at least 60 minutes before a meal.
- The tablets are to be swallowed whole with liquid. Do not split, chew, crush or dissolve the tablet.
- Use the lowest effective dose of YOSPRALA based on the individual patient's treatment goals and to avoid potential dose dependent adverse reactions including bleeding.
- If a dose of YOSPRALA is missed, advise patients to take it as soon as it is remembered. If it is almost time for the next dose, skip the missed dose. Take the next dose at the regular time. Patients should not take 2 doses at the same time unless advised by their doctor.
- Do not stop taking YOSPRALA suddenly as this could increase the risk of heart attack or stroke.

3 DOSAGE FORMS AND STRENGTHS

Oval, blue-green, film-coated, delayed-release tablets for oral administration containing either:

- 81 mg delayed-release aspirin and 40 mg immediate-release omeprazole, printed with 81/40, or
- 325 mg delayed-release aspirin and 40 mg immediate-release omeprazole, printed with 325/40.

4 CONTRAINDICATIONS

YOSPRALA is contraindicated in:

- Patients with known allergy to aspirin and other nonsteroidal anti-inflammatory drug products (NSAIDs) and in patients with the syndrome of asthma, rhinitis, and nasal polyps. Aspirin may cause severe urticaria, angioedema, or bronchospasm (asthma).
- Pediatric patients with suspected viral infections, with or without fever, because of the risk of Reye's syndrome with concomitant use of aspirin in certain viral illnesses.
- YOSPRALA is contraindicated in patients with known hypersensitivity to aspirin, omeprazole, substituted benzimidazoles, or to any of the excipients in the formulation [see Warnings and Precautions (5.8), Adverse Reactions (6.2)].
- Proton pump inhibitor (PPI)–containing products, including YOSPRALA, are contraindicated in patients receiving rilpivirine-containing products [see Drug Interactions (7)].

5 WARNINGS AND PRECAUTIONS

5.1 Coagulation Abnormalities

Even low doses of aspirin can inhibit platelet function leading to an increase in bleeding time. This can adversely affect patients with inherited (hemophilia) or acquired (liver disease or vitamin K deficiency) bleeding disorders. Monitor patients for signs of increased bleeding.

5.2 Gastrointestinal Adverse Reactions

Aspirin is associated with serious gastrointestinal (GI) adverse reactions, including inflammation, bleeding ulceration and perforation of the upper and lower GI tract. Other adverse reactions with aspirin include stomach pain, heartburn, nausea, and vomiting.

Serious GI adverse reactions reported in the clinical trials of YOSPRALA were: gastric ulcer hemorrhage in one of the 521 patients treated with YOSPRALA and duodenal ulcer hemorrhage in one of the 524 patients treated with enteric-coated aspirin. In addition, there were two cases of intestinal hemorrhage, one in each treatment group, and one patient treated with YOSPRALA experienced obstruction of the small bowel.

Although minor upper GI symptoms, such as dyspepsia, are common and can occur anytime during therapy, monitor patients for signs of ulceration and bleeding, even in the absence of previous GI symptoms. Inform patients about the signs and symptoms of GI adverse reactions.

If active and clinically significant bleeding from any source occurs in patients receiving YOSPRALA, discontinue treatment.

5.3 Bleeding Risk with Use of Alcohol

Counsel patients who consume three or more alcoholic drinks every day about the bleeding risks involved with chronic, heavy alcohol use while taking YOSPRALA.

5.4 Interaction with Clopidogrel

Avoid concomitant use of YOSPRALA with clopidogrel. Clopidogrel is a prodrug. Inhibition of platelet aggregation by clopidogrel is entirely due to an active metabolite. The metabolism of clopidogrel to its active metabolite can be impaired by use with concomitant medications, such as omeprazole, that interfere with CYP2C19 activity. Co-administration of clopidogrel with 80 mg omeprazole reduces the pharmacological activity of clopidogrel, even when administered 12 hours apart. When using YOSPRALA, consider alternative anti-platelet therapy [see Drug Interactions (7), Clinical Pharmacology (12.3)].

5.5 Interaction with Ticagrelor

Maintenance doses of aspirin above 100 mg reduce the effectiveness of ticagrelor in preventing thrombotic cardiovascular events. Avoid concomitant use of ticagrelor with the 325 mg/40 mg tablet strength of YOSPRALA [see Drug Interactions (7)].

5.6 Renal Failure

Avoid YOSPRALA in patients with severe renal failure (glomerular filtration rate less than 10 mL/minute). Regular use of aspirin is associated in a dose-dependent manner with an increased risk of chronic renal failure. Aspirin use decreases glomerular filtration rate and renal blood flow especially with patients with pre-existing renal disease. [see Use in Specific Populations (8.6), Clinical Pharmacology (12.3)].

5.7 Presence of Gastric Malignancy

In adults, response to gastric symptoms with YOSPRALA does not preclude the presence of gastric malignancy. Consider additional gastrointestinal follow-up and diagnostic testing in adult patients who experience gastric symptoms during treatment with YOSPRALA or have a symptomatic relapse after completing treatment. In older patients, also consider an endoscopy.

5.8 Acute Interstitial Nephritis

Acute interstitial nephritis has been observed in patients taking PPIs including omeprazole. Acute interstitial nephritis may occur at any point during PPI therapy and is generally attributed to an idiopathic hypersensitivity reaction. Discontinue YOSPRALA if acute interstitial nephritis develops [see Contraindications (4)].

5.9 Clostridium difficile-Associated Diarrhea

Published observational studies suggest that PPI-containing therapy like YOSPRALA may be associated with an increased risk of Clostridium difficile-associated diarrhea (CDAD), especially in hospitalized patients. This diagnosis should be considered for diarrhea that does not improve [see Adverse Reactions (6.2)].

Use the lowest dose and shortest duration of YOSPRALA appropriate to the condition being treated.

5.10 Bone Fracture

Several published observational studies suggest that PPI therapy may be associated with an increased risk for osteoporosis-related fractures of the hip, wrist, or spine. The risk of fracture was increased in patients who received high-dose, defined as multiple daily doses, and long-term PPI therapy (a year or longer). Use the lowest dose and shortest duration of YOSPRALA therapy appropriate to the condition being treated. Manage patients at risk for osteoporosis-related fractures according to established treatment guidelines [see Adverse Reactions (6.2)].

5.11 Cutaneous and Systemic Lupus Erythematosus

Cutaneous lupus erythematosus (CLE) and systemic lupus erythematosus (SLE) have been reported in patients taking PPIs, including omeprazole. These events have occurred as both new onset and an exacerbation of existing autoimmune disease. The majority of PPI-induced lupus erythematous cases were CLE.

The most common form of CLE reported in patients treated with PPIs was subacute CLE (SCLE), and occurred within weeks to years after continuous drug therapy in patients ranging from infants to the elderly.Generally, histological findings were observed without organ involvement.

Systemic lupus erythematosus (SLE) is less commonly reported than CLE in patients receiving PPIs. PPI associated SLE is usually milder than non-drug induced SLE. Onset of SLE typically occurred within days to years after initiating treatment, but some cases occurred days or years after initiating treatment. SLE occurred primarily in patients ranging from young adults to the elderly. The majority of patients presented with rash; however, arthralgia and cytopenia were also reported.

Avoid administration of PPIs for longer than medically indicated. If signs or symptoms consistent with CLE or SLE are noted in patients receiving YOSPRALA, discontinue the drug and refer the patient to the appropriate specialist for evaluation. Most patients improve with discontinuation of the PPI alone in 4 to 12 weeks. Serologicial testing (e.g., ANA) may be positive and elevated serologicial test results may take longer to resolve than clinical manifestations.

5.12 Hepatic Impairment

Long-term moderate to high doses of aspirin may result in elevations in serum ALT levels. These abnormalities resolve rapidly with discontinuation of aspirin. The hepatotoxicity of aspirin is usually mild and asymptomatic. Bilirubin elevations are usually mild or absent. Systemic exposure to omeprazole is increased in patients with hepatic impairment [see Clinical Pharmacology (12.3)]. Avoid YOSPRALA in patients with any degree of hepatic impairment [see Use in Specific Populations (8.7)].

5.13 Cyanocobalamin (Vitamin B-12) Deficiency

Daily treatment with any acid-suppressing medications over a long period of time (e.g., longer than 3 years) may lead to malabsorption of cyanocobalamin (vitamin B-12) caused by hypo- or achlorhydria. Rare reports of cyanocobalamin deficiency occurring with acid-suppressing therapy have been reported in the literature. This diagnosis should be considered if clinical symptoms consistent with cyanocobalamin deficiency are observed in patients treated with YOSPRALA.

5.14 Hypomagnesemia

Hypomagnesemia, symptomatic and asymptomatic, has been reported rarely in patients treated with PPIs for at least three months, in most cases after a year of therapy. Serious adverse events include tetany, arrhythmias, and seizures. In most patients, treatment of hypomagnesemia required magnesium replacement and discontinuation of the PPI. For patients expected to be on prolonged treatment or who take YOSPRALA with medications such as digoxin or drugs that may cause hypomagnesemia (e.g., diuretics), consider monitoring magnesium levels prior to initiation of YOSPRALA and periodically during treatment [see Adverse Reactions (6.2)].

5.15 Reduced Effect of Omeprazole with St. John's Wort or Rifampin

Drugs which induce the CYP2C19 or CYP3A4 (such as St. John's Wort or rifampin) can substantially decrease concentrations of omeprazole. Avoid concomitant use of YOSPRALA with St. John's Wort or rifampin [see Drug Interactions (7)].

5.16 Interactions with Diagnostic Investigations for Neuroendocrine Tumors

Serum chromogranin A (CgA) levels increase secondary to omeprazole-induced decreases in gastric acidity. The increased CgA level may cause false positive results in diagnostic interventions for neuroendocrine tumors. Temporarily discontinue treatment with YOSPRALA at least 14 days before assessing CgA levels and consider repeating the test if initial CgA levels are high. If serial tests are performed (e.g., for monitoring), the same commercial laboratory should be used for testing, as reference ranges between tests may vary [see Drug Interactions (7) and Clinical Pharmacology (12.2)].

5.17 Interaction with Methotrexate

Literature suggests that concomitant use of PPIs with methotrexate (primarily at high dose) may elevate and prolong serum levels of methotrexate and/or its metabolite, possibly leading to methotrexate toxicities. In high-dose methotrexate administration, a temporary withdrawal of YOSPRALA may be considered in some patients [see Drug Interactions (7)].

5.18 Premature Closure of Fetal Ductus Arteriosus

NSAIDs including aspirin, may cause premature closure of the fetal ductus arteriosus. Avoid use of NSAIDs, including YOSPRALA, in pregnant women starting at 30 weeks of gestation (third trimester). [see Use in Specific Populations (8.1)].

5.19 Abnormal Laboratory Tests

Aspirin has been associated with elevated hepatic enzymes, blood urea nitrogen and serum creatinine, hyperkalemia, proteinuria, and prolonged bleeding time.

5.20 Fundic Gland Polyps

PPI use is associated with an increased risk of fundic gland polyps that increases with long-term use, especially beyond one year. Most PPI users who developed fundic gland polyps were asymptomatic and fundic gland polyps were identified incidentally on endoscopy. Use the shortest duration of PPI therapy appropriate to the condition being treated.

7 DRUG INTERACTIONS

Tables 2 and 3 include drugs with clinically important drug interactions and interaction with diagnostics when administered concomitantly with YOSPRALA and instructions for preventing or managing them.

Consult the labeling of concomitantly used drugs to obtain further information about interactions with omeprazole or aspirin.

Table 2: Clinically Relevant Interactions Affecting Drugs Co-Administered with YOSPRALA and Interaction with Diagnostics
Antiretrovirals
Clinical Impact: | The effect of PPIs, such as omeprazole, on antiretroviral drugs is variable. The clinical importance and the mechanisms behind these interactions are not always known.; - Decreased exposure of some antiretroviral drugs (e.g., rilpivirine, atazanavir and nelfinavir) when used concomitantly with omeprazole may reduce antiviral effect and promote the development of drug resistance [see Clinical Pharmacology (12.3)]. - Increased exposure of other antiretroviral drugs (e.g., saquinavir) when used concomitantly with omeprazole may increase toxicity [see Clinical Pharmacology (12.3)]. - There are other antiretroviral drugs which do not result in clinically relevant interactions with omeprazole.
Intervention: | Rilpivirine-containing products: Concomitant use with YOSPRALA is contraindicated [see Contraindications (4)]. Atazanavir: Avoid concomitant use with YOSPRALA. See prescribing information for atazanavir for dosing information. Nelfinavir: Avoid concomitant use with YOSPRALA. See prescribing information for nelfinavir. Saquinavir: See the prescribing information for saquinavir for monitoring of potential saquinavir-related toxicities. Other antiretrovirals: See prescribing information for specific antiretroviral drugs.
Heparin and Warfarin
Clinical Impact: | Increased INR and prothrombin time in patients receiving PPIs, including omeprazole, and warfarin concomitantly. Increases in INR and prothrombin time may lead to abnormal bleeding and even death. Aspirin can increase the anticoagulant activity of heparin and warfarin, increasing bleeding risk.
Intervention: | Monitor INR and prothrombin time and adjust the dose of warfarin, if needed, to maintain target INR range. Monitor and adjust the dose of heparin and warfarin as needed.
Methotrexate
Clinical Impact: | Concomitant use of omeprazole with methotrexate (primarily at high dose) may elevate and prolong serum concentrations of methotrexate and/or its metabolite hydroxymethotrexate, possibly leading to methotrexate toxicities. No formal drug interaction studies of high-dose methotrexate with PPIs, such as omeprazole, have been conducted [see Warnings and Precautions (5.17)].
Intervention: | A temporary withdrawal of YOSPRALA may be considered in some patients receiving high-dose methotrexate.
CYP2C19 Substrates (e.g., clopidogrel, citalopram, cilostazol, phenytoin, diazepam)
Clopidogrel
Clinical Impact: | Concomitant use of omeprazole 80 mg results in reduced plasma concentrations of the active metabolite of clopidogrel and a reduction in platelet inhibition [see Clinical Pharmacology (12.3)]. There are no adequate combination studies of a lower dose of omeprazole or a higher dose of clopidogrel in comparison with the approved dose of clopidogrel.
Intervention: | Avoid concomitant use with YOSPRALA. Consider use of alternative anti-platelet therapy [see Warnings and Precautions (5.4)].
Citalopram
Clinical Impact: | Concomitant use of omeprazole results in increased exposure of citalopram leading to an increased risk of QT prolongation [see Clinical Pharmacology (12.3)].
Intervention: | Limit the dose of citalopram to a maximum of 20 mg per day. See prescribing information for citalopram.
Cilostazol
Clinical Impact: | Concomitant use of omeprazole results in increased exposure of one of the active metabolites of cilostazol (3,4-dihydro-cilostazol).
Intervention: | Reduce the dose of cilostazol to 50 mg twice daily. See prescribing information for cilostazol.
Phenytoin
Clinical Impact: | Potential for increased exposure of phenytoin with concomitant omeprazole. Aspirin can displace protein-bound phenytoin leading to a decrease in the total concentration of phenytoin.
Intervention: | Monitor phenytoin serum concentrations. Dose adjustment may be needed to maintain therapeutic drug concentrations. See prescribing information for phenytoin.
Diazepam
Clinical Impact: | Increased exposure of diazepam with concomitant omeprazole [see Clinical Pharmacology (12.3)].
Intervention: | Monitor patients for increased sedation and reduce the dose of diazepam as needed.
Ticagrelor
Clinical Impact: | Maintenance doses of aspirin above 100 mg reduce the effectiveness of ticagrelor.
Intervention: | Avoid concomitant use of ticagrelor with the 325 mg/40 mg tablet strength of YOSPRALA [see Warnings and Precautions (5.5)].
Digoxin
Clinical Impact: | Potential for increased exposure of digoxin with concomitant omeprazole [see Clinical Pharmacology (12.3)].
Intervention: | Monitor digoxin concentrations. Dose adjustment may be needed to maintain therapeutic drug concentrations. See digoxin prescribing information.
Drugs Dependent on Gastric pH for Absorption (e.g., iron salts, erlotinib, dasatinib, nilotinib, mycophenolate mofetil, ketoconazole/itraconazole)
Clinical Impact: | Omeprazole can reduce the absorption of other drugs due to its effect on reducing intragastric acidity.
Intervention: | Mycophenolate mofetil (MMF): Co-administration of omeprazole in healthy subjects and in transplant patients receiving MMF has been reported to reduce the exposure to the active metabolite, mycophenolic acid (MPA), possibly due to a decrease in MMF solubility at an increased gastric pH. The clinical relevance of reduced MPA exposure on organ rejection has not been established in transplant patients receiving omeprazole and MMF. Use Yosprala with caution in transplant patients receiving MMF [see Clinical Pharmacology (12.3)]. See the prescribing information for other drugs dependent on gastric pH for absorption.
Tacrolimus
Clinical Impact: | Potential for increased exposure of tacrolimus with concomitant omeprazole, especially in transplant patients who are intermediate or poor metabolizers of CYP2C19.
Intervention: | Monitor tacrolimus whole blood concentrations. Dose adjustment may be needed to maintain therapeutic drug concentrations. See prescribing information for tacrolimus.
ACE-Inhibitors
Clinical Impact: | Aspirin may diminish the antihypertensive effect of ACE-inhibitors.
Intervention: | Monitor blood pressure as needed.
Beta Blockers
Clinical Impact: | The hypotensive effects of beta blockers may be diminished by the concomitant administration of aspirin.
Intervention: | Monitor blood pressure as needed in patients taking YOSPRALA concomitantly with beta blockers for hypertension.
Diuretics
Clinical Impact: | The effectiveness of diuretics in patients with underlying renal or cardiovascular disease may be diminished by the concomitant administration of aspirin.
Intervention: | Monitor blood pressure as needed.
NSAIDs
Clinical Impact: | The concurrent use of NSAIDs and aspirin may increase the risk of serious adverse events, including increased bleeding or decreased renal function.
Intervention: | Monitor for signs and symptoms of bleeding or decreased renal function.
Oral Hypoglycemics
Clinical Impact: | Moderate doses of aspirin may increase the effectiveness of oral hypoglycemic drugs, leading to hypoglycemia.
Intervention: | Monitor blood sugar as needed.
Acetazolamide
Clinical Impact: | Concurrent use of aspirin and acetazolamide can lead to high serum concentrations of acetazolamide (and toxicity).
Intervention: | Adjust the dose of acetazolamide if signs of toxicity occur.
Uricosuric Agents (Probenecid)
Clinical Impact: | Aspirin antagonizes the uricosuric action of uricosuric agents.
Intervention: | Monitor serum uric acid levels as needed.
Valproic Acid
Clinical Impact: | Concomitant use of aspirin can displace protein-bound valproic acid, leading to an increase in serum concentrations of valproic acid.
Intervention: | Monitor valproic acid serum concentrations. Dose adjustment may be needed to maintain therapeutic drug concentrations. See prescribing information for valproic acid.
Interactions with Investigations of Neuroendocrine Tumors
Clinical Impact: | Serum chromogranin A (CgA) levels increase secondary to omeprazole-induced decreases in gastric acidity. The increased CgA level may cause false positive results in diagnostic investigations for neuroendocrine tumors [see Warnings and Precautions (5.16), Clinical Pharmacology (12.2)].
Intervention: | Temporarily stop YOSPRALA treatment at least 14 days before assessing CgA levels and consider repeating the test if initial CgA levels are high. If serial tests are performed (e.g., for monitoring), the same commercial laboratory should be used for testing, as reference ranges between tests may vary.
Interaction with Secretin Stimulation Test
Clinical Impact: | Omeprazole can cause a hyper-response in gastrin secretion in response to secretin stimulation test, falsely suggesting gastrinoma.
Intervention: | Temporarily stop YOSPRALA treatment at least 14 days before assessing to allow gastrin levels to return to baseline [see Clinical Pharmacology (12.2)].
False Positive Urine Tests for THC
Clinical Impact: | There have been reports of false positive urine screening tests for tetrahydrocannabinol (THC) in patients receiving PPIs such as omeprazole.
Intervention: | An alternative confirmatory method should be considered to verify positive results.
Other
Clinical Impact: | There have been clinical reports of interactions with other drugs metabolized via the cytochrome P450 system (e.g., cyclosporine, disulfiram) with omeprazole.
Intervention: | Monitor patients to determine if it is necessary to adjust the dosage of these other drugs when taken concomitantly with YOSPRALA.

Table 3: Clinically Relevant Interactions Affecting YOSPRALA When Co- Administered with Other Drugs
CYP2C19 or CYP3A4 Inducers
Clinical Impact: | Decreased exposure of omeprazole when used concomitantly with strong inducers [see Clinical Pharmacology (12.3)].
Intervention: | St. John's Wort, rifampin: Avoid concomitant use with YOSPRALA [see Warnings and Precautions (5.15)]. Ritonavir-containing products: See prescribing information for specific drugs.
CYP2C19 or CYP3A4 Inhibitors
Clinical Impact: | Increased exposure of omeprazole [see Clinical Pharmacology (12.3)].
Intervention: | Voriconazole: Avoid concomitant use with YOSPRALA.

8 USE IN SPECIFIC POPULATIONS

8.1 Pregnancy

Risk Summary

Use of NSAIDs, including YOSPRALA, during the third trimester of pregnancy increases the risk of premature closure of the fetal ductus arteriosus. Avoid use of NSAIDs, including YOSPRALA, in pregnant women starting at 30 weeks of gestation (third trimester). There are no available data with YOSPRALA use in pregnant women to inform a drug-associate risk for major birth defects and miscarriage; however, there are published studies with each individual component of YOSPRALA.

Aspirin

Data from controlled and observational studies with aspirin use during pregnancy have not reported a clear association with major birth defects or miscarriage risk. However, NSAIDs, including aspirin, a component of YOSPRALA, may increase the risk of complications during labor or delivery and to the neonate [see Clinical Considerations and Data]. In animal reproduction studies, there were adverse developmental effects with oral administration of aspirin to pregnant rats at doses 15 to 19 times the maximum recommended human dose (MRHD) of 325 mg/day. Aspirin did not produce adverse developmental effects in rabbits [see Data].

Omeprazole

Data from epidemiological and observational studies with omeprazole have not reported a clear association with major birth defects or miscarriage risk. Animal reproduction studies in pregnant rats and rabbits resulted in dose-dependent embryo-lethality at omeprazole doses that were approximately 3.4 to 34 times an oral human dose of 40 mg.

Changes in bone morphology were observed in offspring of rats dosed through most of pregnancy and lactation at doses equal to or greater than approximately 34 times an oral human dose of 40 mg esomeprazole or 40 mg omeprazole. When maternal administration was confined to gestation only, there were no effects on bone physeal morphology in the offspring at any age [see Data].

The estimated background risks of major birth defects and miscarriage for the indicated population are unknown. All pregnancies have a background risk of birth defect, loss or other adverse outcomes. In the U.S. general population, the estimated background risk of major birth defects and miscarriage in clinically recognized pregnancies is 2% to 4% and 15% to 20%, respectively.

Clinical Considerations

Fetal/Neonatal Adverse Reactions

Maternal aspirin use during the third trimester of pregnancy may increase the risk of neonatal complications, including necrotizing enterocolitis, patent ductus arteriosus, intracranial hemorrhage in premature infants, low birth weight, stillbirth and neonatal death.

Maternal Adverse Reactions

An increased incidence of post-term pregnancy and longer duration of pregnancy in women taking aspirin has been reported. Avoid maternal use of aspirin, including Yosprala, in pregnant women during the third trimester.

Labor or Delivery

Aspirin, a component of YOSPRALA, should be avoided 1 week prior to and during labor and delivery because it can result in excessive blood loss at delivery. In animal studies, NSAIDS, including aspirin, inhibit prostaglandin synthesis, cause delayed parturition, and increase the incidence of stillbirth.

Data

Human Data

Aspirin

Data from several controlled and observational studies with aspirin use in the first or second trimesters of pregnancy have not reported a clear association with major birth defects or miscarriage risk. Published data on aspirin use during pregnancy has been mostly reported with low dose aspirin (60 to 100 mg). There are limited data regarding aspirin 325 mg or higher doses used during pregnancy.

A prospective, cohort study of 50,282 mother-child pairs (the Collaborative Perinatal Project) assessing adverse outcomes by level of aspirin exposure did not report aspirin-induced teratogenicity, altered neonatal birth weight, or perinatal deaths at any exposure level. In a controlled, randomized trial, maternal risks during pregnancy were reported as low or absent, with no demonstrated increased risk of maternal bleeding or placental abruptio. A multinational study involving more than 9,000 women, CLASP (Collaborative Low-dose Aspirin Study in Pregnancy)], found that low-dose aspirin reduced fetal morbidity in a select population of women with early-onset preeclampsia, but did not identify adverse effects in the pregnant woman, fetus, or newborn (followed to 12 and 18 months of age) in association with the use of low-dose aspirin during pregnancy. In contrast, some case-control studies reported associations between human congenital malformations and aspirin use early in gestation, but these studies did not report a consistent outcome attributable to drug use.

A report from EAGeR trial (Effects of Aspirin in Gestation and Reproduction trial), which evaluated 1078 women who were attempting to become pregnant and had prior miscarriages, reported use of low-dose aspirin without adverse maternal or fetal effects except for vaginal bleeding. Another trial of 3294 pregnant women of 14 to 20 weeks of gestation treated with aspirin showed no effect in the mothers' incidence of pre-eclampsia, hypertension, HELLP syndrome or placental abruptio, or in the incidence of perinatal deaths or low birth weight below the 10th percentile. The incidence of maternal side effects was higher in the aspirin group, principally because of a significantly higher rate of hemorrhage.

Use of NSAIDs, including aspirin, during the third trimester of pregnancy increases the risk of premature closure of the fetal ductus arteriosus and use of high-dose aspirin for long periods in pregnancy may also increase the risk of bleeding in the brain of premature infants.

Omeprazole

Four published epidemiological studies compared the frequency of congenital abnormalities among infants born to women who used omeprazole during pregnancy with the frequency of abnormalities among infants of women exposed to H2-receptor antagonists or other controls.

A population-based retrospective cohort epidemiological study from the Swedish Medical Birth Registry, covering approximately 99% of pregnancies, from 1995 to 1999, reported on 955 infants (824 exposed during the first trimester with 39 of these exposed beyond first trimester, and 131 exposed after the first trimester) whose mothers used omeprazole during pregnancy. The number of infants exposed in utero to omeprazole that had any malformation, low birth weight, low Apgar score, or hospitalization was similar to the number observed in this population. The number of infants born with ventricular septal defects and the number of stillborn infants was slightly higher in the omeprazole-exposed infants than the expected number in this population.

A population-based retrospective cohort study covering all live births in Denmark from 1996 to 2009, reported on 1,800 live births whose mothers used omeprazole during the first trimester of pregnancy and 837,317 live births whose mothers did not use any PPI. The overall rate of birth defects in infants born to mothers with first trimester exposure to omeprazole was 2.9% and 2.6% in infants born to mothers not exposed to any proton pump inhibitor during the first trimester.

A retrospective cohort study reported on 689 pregnant women exposed to either H2-blockers or omeprazole in the first trimester (134 exposed to omeprazole) and 1,572 pregnant women unexposed to either during the first trimester. The overall malformation rate in offspring born to mothers with first trimester exposure to omeprazole, an H2-blocker, or were unexposed was 3.6%, 5.5%, and 4.1% respectively.

A small prospective observational cohort study followed 113 women exposed to omeprazole during pregnancy (89% with first trimester exposures). The reported rate of major congenital malformations was 4% in the omeprazole group, 2% in controls exposed to non-teratogens, and 2.8% in disease-paired controls. Rates of spontaneous and elective abortions, preterm deliveries, gestational age at delivery, and mean birth weight were similar among the groups.

Several studies have reported no apparent adverse short-term effects on the infant when single dose oral or intravenous omeprazole was administered to over 200 pregnant women as premedication for cesarean section under general anesthesia.

Animal Data

Aspirin

Aspirin produced a spectrum of developmental anomalies when administered to Wistar rats as single, large doses (500 to 625 mg/kg) on gestational day (GD) 9, 10, or 11. These doses (500 to 625 mg/kg) in rats are about 15 to 19 times the maximum recommended human dose of aspirin (325 mg/day) based on body surface area. Many of the anomalies were related to closure defects and included craniorachischisis, gastroschisis and umbilical hernia, and cleft lip, in addition to diaphragmatic hernia, heart malrotation, and supernumerary ribs and kidneys. In contrast to the rat, aspirin was not developmentally toxic in rabbits.

Omeprazole

Reproductive studies conducted with omeprazole in rats at oral doses up to 138 mg/kg/day (about 34 times an oral human dose of 40 mg on a body surface area basis) and in rabbits at doses up to 69.1 mg/kg/day (about 34 times an oral human dose of 40 mg on a body surface area basis) during organogenesis did not disclose any evidence for a teratogenic potential of omeprazole. In rabbits, omeprazole in a dose range of 6.9 to 69.1 mg/kg/day (about 3.4 to 34 times an oral human dose of 40 mg on a body surface area basis) administered during organogenesis produced dose-related increases in embryo-lethality, fetal resorptions, and pregnancy disruptions. In rats, dose-related embryo/fetal toxicity and postnatal developmental toxicity were observed in offspring resulting from parents treated with omeprazole at 13.8 to 138 mg/kg/day (about 3.4 to 34 times an oral human doses of 40 mg on a body surface area basis), administered prior to mating through the lactation period.

Esomeprazole

The data described below was generated from studies using esomeprazole, an enantiomer of omeprazole. The animal to human dose multiples are based on the assumption of equal systemic exposure to esomeprazole in humans following oral administration of either 40 mg esomeprazole or 40 mg omeprazole.

No effects on embryo-fetal development were observed in reproduction studies with esomeprazole magnesium in rats at oral doses up to 280 mg/kg/day (about 68 times an oral human dose of 40 mg on a body surface area basis) or in rabbits at oral doses up to 86 mg/kg/day (about 42 times an oral human dose of 40 mg esomeprazole or 40 mg omeprazole on a body surface area basis) administered during organogenesis.

A pre- and postnatal developmental toxicity study in rats with additional endpoints to evaluate bone development was performed with esomeprazole magnesium at oral doses of 14 to 280 mg/kg/day (about 3.4 to 68 times an oral human dose of 40 mg esomeprazole or 40 mg omeprazole on a body surface area basis). Neonatal/early postnatal (birth to weaning) survival was decreased at doses equal to or greater than 138 mg/kg/day (about 34 times an oral human dose of 40 mg esomeprazole or 40 mg omeprazole on a body surface area basis). Body weight and body weight gain were reduced and neurobehavioral or general developmental delays in the immediate post-weaning timeframe were evident at doses equal to or greater than 69 mg/kg/day (about 17 times an oral human dose of 40 mg esomeprazole or 40 mg omeprazole on a body surface area basis). In addition, decreased femur length, width and thickness of cortical bone, decreased thickness of the tibial growth plate and minimal to mild bone marrow hypocellularity were noted at doses equal to or greater than 14 mg/kg/day (about 3.4 times an oral human dose of 40 mg esomeprazole or 40 mg omeprazole on a body surface area basis).

Physeal dysplasia in the femur was observed in offspring of rats treated with oral doses of esomeprazole magnesium at doses equal to or greater than 138 mg/kg/day (about 34 times an oral human dose of 40 mg esomeprazole or 40 mg omeprazole on a body surface area basis).

Effects on maternal bone were observed in pregnant and lactating rats in the pre- and postnatal toxicity study when esomeprazole magnesium was administered at oral doses of 14 to 280 mg/kg/day (about 3.4 to 68 times an oral human dose of 40 mg esomeprazole or 40 mg omeprazole on a body surface area basis). When rats were dosed from gestational day 7 through weaning on postnatal day 21, a statistically significant decrease in maternal femur weight of up to 14% (as compared to placebo treatment) was observed at doses equal to or greater than 138 mg/kg/day (about 34 times an oral human dose of 40 mg esomeprazole or 40 mg omeprazole on a body surface area basis).

A pre- and postnatal development study in rats with esomeprazole strontium (using equimolar doses compared to esomeprazole magnesium study) produced similar results in dams and pups as described above.

A follow up developmental toxicity study in rats with further time points to evaluate pup bone development from postnatal day 2 to adulthood was performed with esomeprazole magnesium at oral doses of 280 mg/kg/day (about 68 times an oral human dose of 40 mg on a body surface area basis) where esomeprazole administration was from either gestational day 7 or gestational day 16 until parturition. When maternal administration was confined to gestation only, there were no effects on bone physeal morphology in the offspring at any age.

8.2 Lactation

Risk Summary

There is no information about the presence of YOSPRALA in human milk; however, the individual components of YOSPRALA, aspirin and omeprazole, are present in human milk. Limited data from clinical lactation studies in published literature describe the presence of aspirin in human milk at relative infant doses of 2.5% to 10.8% of the maternal weight-adjusted dosage. Case reports of breastfeeding infants whose mothers were exposed to aspirin during lactation describe adverse reactions, including metabolic acidosis, thrombocytopenia, and hemolysis. There is no information on the effects of aspirin on milk production. Limited data from a case report in published literature describes the presence of omeprazole in human milk at a relative infant dose of 0.9% of the maternal weight-adjusted dosage. There are no reports of adverse effects of omeprazole on the breastfed infant, and no information on the effects of omeprazole on milk production. Because of the potential for serious adverse reactions, including the potential for aspirin to cause metabolic acidosis, thrombocytopenia, hemolysis or Reye's syndrome, advise patients that breastfeeding is not recommended during treatment with YOSPRALA.

Clinical Considerations

It is not known if maternal exposure to aspirin during lactation increases the risk of Reye's syndrome in breastfed infants. The direct use of aspirin in infants and children is associated with Reye's syndrome, even at low plasma levels.

8.3 Females and Males of Reproductive Potential

Infertility

Females

Based on the mechanism of action, the use of prostaglandin-mediated NSAIDs, including YOSPRALA, may delay or prevent rupture of ovarian follicles, which has been associated with reversible infertility in some women. Published animal studies have shown that administration of prostaglandin synthesis inhibitors has the potential to disrupt prostaglandin-mediated follicular rupture required for ovulation. Small studies in women treated with NSAIDs have also demonstrated a reversible delay in ovulation. Consider withdrawal of NSAIDs, including YOSPRALA, in women who have difficulties conceiving or who are undergoing investigation of infertility.

8.4 Pediatric Use

The safety and efficacy of YOSPRALA has not been established in pediatric patients. YOSPRALA is contraindicated in pediatric patients with suspected viral infections, with or without fever, because of the risk of Reye's syndrome with concomitant use of aspirin in certain viral illnesses [see Contraindications (4)].

Juvenile Animal Data

In a juvenile rat toxicity study, esomeprazole was administered with both magnesium and strontium salts at oral doses about 17 to 67 times a daily human dose of 40 mg based on body surface area. Increases in death were seen at the high dose, and at all doses of esomeprazole, there were decreases in body weight, body weight gain, femur weight and femur length, and decreases in overall growth [see Nonclinical Toxicology (13.2)].

8.5 Geriatric Use

Of the total number of patients who received YOSPRALA (n=900) in clinical trials, 62% were ≥65 years of age and 15% were 75 years and over. No overall differences in safety or effectiveness were observed between these subjects and younger subjects and other reported clinical experience with aspirin and omeprazole has not identified differences in responses between the elderly and younger patients, but greater sensitivity of some older individuals cannot be ruled out [see Clinical Pharmacology (12.3)].

8.6 Renal Impairment

No dose reduction of YOSPRALA is necessary in patients with mild to moderate renal impairment. Avoid YOSPRALA in patients with severe renal impairment (glomerular filtration rate less than 10 mL/minute) due to the aspirin component [see Warnings and Precautions (5.6), Clinical Pharmacology (12.3)].

8.7 Hepatic Impairment

Long-term moderate to high doses of aspirin may result in elevations in serum ALT levels [see Warnings and Precautions (5.12)]. Systemic exposure to omeprazole is increased in patients with hepatic impairment [see Clinical Pharmacology (12.3)]. Avoid YOSPRALA in patients with any degree of hepatic impairment.

8.8 Asian Population

In studies of healthy subjects, Asians had approximately a four-fold higher exposure to omeprazole than Caucasians. CYP2C19, a polymorphic enzyme, is involved in the metabolism of omeprazole. Approximately 15% to 20% of Asians are CYP2C19 poor metabolizers. Tests are available to identify a patient's CYP2C19 genotype. Avoid use in Asian patients with unknown CYP2C19 genotype or those who are known to be poor metabolizers [see Clinical Pharmacology (12.5)].

10 OVERDOSAGE

There is no clinical data on overdosage with YOSPRALA.

Aspirin

Salicylate toxicity may result from acute ingestion (overdose) or chronic intoxication. The early signs of salicylic overdose (salicylism), including tinnitus (ringing in the ears), occur at plasma concentrations approaching 200 mg/mL. Plasma concentrations of aspirin above 300 mg/mL are clearly toxic. Severe toxic effects are associated with levels above 400 mg/mL. A single lethal dose of aspirin in adults is not known with certainty but death may be expected at 30 g.

Signs and Symptoms: In acute overdose, severe acid-base and electrolyte disturbances may occur and are complicated by hyperthermia and dehydration. Respiratory alkalosis occurs early while hyperventilation is present, but is quickly followed by metabolic acidosis.

Treatment: Treatment consists primarily of supporting vital functions, increasing salicylate elimination, and correcting the acid-base disturbance. Gastric emptying and/or lavage is recommended as soon as possible after ingestion, even if the patient has vomited spontaneously. After lavage and/or emesis, administration of activated charcoal, as a slurry, is beneficial, if less than 3 hours have passed since ingestion. Charcoal adsorption should not be employed prior to emesis and lavage.

Severity of aspirin intoxication is determined by measuring the blood salicylate level. Serial salicylate levels should be obtained every 1 to 2 hours until concentrations have peaked and are declining. Acid-base status should be closely followed with serial blood gas and serum pH measurements. Fluid and electrolyte balance should also be maintained.

In severe cases, hyperthermia and hypovolemia are the major immediate threats to life. Children should be sponged with tepid water. Replacement fluid should be administered intravenously and augmented with correction of acidosis. Plasma electrolytes and pH should be monitored to promote alkaline diuresis of salicylate if renal function is normal. Infusion of glucose may be required to control hypoglycemia.

Hemodialysis and peritoneal dialysis can be performed to reduce the body drug content. In patients with renal impairment or in cases of life-threatening intoxication, dialysis is usually required. Exchange transfusion may be indicated in infants and young children.

Omeprazole

Reports have been received of overdosage with omeprazole in humans. Doses ranged up to 2400 mg. Manifestations were variable, but included confusion, drowsiness, blurred vision, tachycardia, nausea, vomiting, diaphoresis, flushing, headache, dry mouth, and other adverse reactions similar to those seen with recommended doses of omeprazole [see Adverse Reactions (6)]. Symptoms were transient, and no serious clinical outcome has been reported when omeprazole was taken alone. No specific antidote for omeprazole overdosage is known. Omeprazole is extensively protein bound and is, therefore, not readily dialyzable. In the event of overdosage, treatment should be symptomatic and supportive.

If overexposure to YOSPRALA occurs, call your Poison Control Center at 1-800-222-1222 for current information on the management of poisoning or overdosage.

11 DESCRIPTION

The active ingredients of YOSPRALA are aspirin which is an antiplatelet agent and omeprazole which is a PPI.

YOSPRALA (aspirin and omeprazole) is an oval, blue-green, multi-layer film-coated, delayed-release tablet consists of an enteric coated delayed-release aspirin core surrounded by an immediate-release omeprazole layer for oral administration. Each delayed-release tablet contains either 81 mg aspirin and 40 mg omeprazole printed with 81/40, or 325 mg aspirin and 40 mg omeprazole printed with 325/40.

The excipients used in the formulation of YOSPRALA are all inactive and United States Pharmacopeia/National Formulary (USP/NF) defined. The inactive ingredients in YOSPRALA include: carnauba wax, colloidal silicon dioxide, corn starch, FD&C Blue #2, glyceryl monostearate, hydroxypropyl methycellulose, methacrylic acid copolymer dispersion, microcrystalline cellulose, polydextrose, polyethylene glycol, polysorbate 80, povidone, pre-gelatinized starch, sodium phosphate dibasic anhydrous, stearic acid, talc, titanium dioxide, triacetin, triethyl citrate, yellow iron oxide.

Aspirin is acetylsalicylic acid and is chemically known as benzoic acid, 2-(acetyloxy). Aspirin is an odorless white needle-like crystalline or powdery substance. When exposed to moisture, aspirin hydrolyzes into salicylic and acetic acids and gives off a vinegary odor. It is highly lipid soluble and slightly soluble in water. Aspirin irreversibly inhibits platelet COX-1.

Omeprazole is a white to off-white crystalline powder which melts with decomposition at about 155°C. It is a weak base, freely soluble in ethanol and methanol, and slightly soluble in acetone and isopropanol and very slightly soluble in water. The stability of omeprazole is a function of pH; it is rapidly degraded in acid media, but has acceptable stability under alkaline conditions.

Omeprazole is a substituted benzimidazole, 5-methoxy-2-[[(4-methoxy-3, 5-dimethyl-2-pyridinyl) methyl] sulfinyl]-1H- benzimidazole, a compound that inhibits gastric acid secretion.

Structural Formula

Aspirin

Omeprazole

Molecular Formula

The empirical formula of aspirin is C9H8O4.

The empirical formula of omeprazole is C17H19N3O3S.

Molecular Weight

The molecular weight of aspirin is 180.16.

The molecular weight of omeprazole is 345.4.

12 CLINICAL PHARMACOLOGY

12.1 Mechanism of Action

Aspirin (acetylsalicylic acid) is an inhibitor of both prostaglandin synthesis and platelet aggregation. The differences in activity between aspirin and salicylic acid are thought to be due to the acetyl group on the aspirin molecule. This acetyl group is responsible for the inactivation of cyclo-oxygenase via acetylation.

Omeprazole belongs to a class of antisecretory compounds, the substituted benzimidazoles, that suppress gastric acid secretion by specific inhibition of the [H^+/K^+]-ATPase enzyme system at the secretory surface of the gastric parietal cell. Because this enzyme system is regarded as the acid (proton) pump within the gastric mucosa, omeprazole has been characterized as a gastric acid-pump inhibitor, in that it blocks the final step of acid production. This effect is dose-related and leads to inhibition of both basal and stimulated acid secretion irrespective of the stimulus.

12.2 Pharmacodynamics

Anti-platelet Activity

Aspirin affects platelet aggregation by irreversibly inhibiting prostaglandin cyclo-oxygenase. This effect lasts for the life of the platelet and prevents the formation of the platelet aggregating factor thromboxane A2. Nonacetylated salicylates do not inhibit this enzyme and have no effect on platelet aggregation. At higher doses, aspirin reversibly inhibits the formation of prostaglandin I2 (prostacyclin), which is an arterial vasodilator and inhibits platelet aggregation.

Antisecretory Activity

The effect of YOSPRALA 325 mg/40 mg tablets on intragastric pH was determined in a study of 26 healthy subjects dosed for 7 days. The mean percent time intragastric pH >4.0 was 51%.

Serum Gastrin Effects

In studies involving more than 200 patients, serum gastrin levels increased during the first 1 to 2 weeks of once-daily administration of therapeutic doses of omeprazole in parallel with inhibition of acid secretion. No further increase in serum gastrin occurred with continued treatment. In comparison with histamine H2-receptor antagonists, the median increases produced by 20 mg doses of omeprazole were higher (1.3 to 3.6 fold vs. 1.1 to 1.8 fold increase). Gastrin values returned to pretreatment levels, usually within 1 to 2 weeks after discontinuation of therapy.

Increased gastrin causes enterochromaffin-like cell hyperplasia and increased serum Chromogranin A (CgA) levels. The increased CgA levels may cause false positive results in diagnostic investigations for neuroendocrine tumors [see Warnings and Precautions (5.16), Drug Interactions (7)].

Enterochromaffin-like (ECL) Cell Effects

Human gastric biopsy specimens have been obtained from more than 3000 patients treated with omeprazole in long-term clinical trials. The incidence of ECL cell hyperplasia in these studies increased with time; however, no case of ECL cell carcinoids, dysplasia, or neoplasia has been found in these patients. However, these studies are of insufficient duration and size to rule out the possible influence of long-term administration of omeprazole on the development of any premalignant or malignant conditions.

Endocrine Effects

Omeprazole given in oral doses of 30 or 40 mg for 2 to 4 weeks had no effect on thyroid function, carbohydrate metabolism, circulating levels of parathyroid hormone, cortisol, estradiol, testosterone, prolactin, cholecystokinin or secretin.

Effects on Gastrointestinal Microbial Ecology

As do other agents that elevate intragastric pH, omeprazole administered for 14 days in healthy subjects produced a significant increase in the intragastric concentrations of viable bacteria. The pattern of the bacterial species was unchanged from that commonly found in saliva. All changes resolved within three days of stopping treatment.

Other Effects

Systemic effects of omeprazole in the CNS, cardiovascular and respiratory systems have not been found to date.

No effect on gastric emptying of the solid and liquid components of a test meal was demonstrated after a single dose of omeprazole 90 mg. In healthy subjects, a single intravenous dose of omeprazole (0.35 mg/kg) had no effect on intrinsic factor secretion. No systematic dose-dependent effect has been observed on basal or stimulated pepsin output in humans. However, when intragastric pH is maintained at 4.0 or above, basal pepsin output is low, and pepsin activity is decreased.

12.3 Pharmacokinetics

Absorption

Aspirin: Following absorption, aspirin (acetylsalicylic acid) is hydrolyzed to salicylic acid. The rate of absorption from the GI tract is dependent upon the presence or absence of food, gastric pH (the presence or absence of GI antacids or buffering agents), and other physiologic factors. Enteric coated aspirin products are erratically absorbed from the GI tract.

Following single dose administration of YOSPRALA, peak concentrations of acetylsalicylic acid were reached at 2.5 hours for YOSPRALA 81 mg/40 mg tablets and at 4 to 4.5 hours for YOSPRALA 325 mg/40 mg tablets. The Cmax and AUC of acetylsalicylic acid were 2.6 mcg/mL and 3 mcg.hr/mL following single dose administration of YOSPRALA 81 mg/40 mg tablets and were 2.5 mcg/mL and 2.9 mcg.hr/mL following single dose administration of YOSPRALA 325 mg/40 mg tablets. There is no significant accumulation of salicylic acid and acetylsalicylic acid following 7 days dosing of YOSPRALA 325 mg/40 mg tablets compared to the first day of dosing.

The inter-subject variability (CV%) of acetylsalicylic acid pharmacokinetic parameters ranged from 17% to 96%.

Omeprazole: Following administration of YOSPRALA, the peak plasma concentration of omeprazole is reached at 0.5 hours on both the first day of administration and at steady state. The Cmax and AUC of omeprazole ranged from 617 to 856 ng/mL and 880-1384 ng.hr/mL following single dose administration of YOSPRALA 325 mg/40 mg tablets. Dosing YOSPRALA 325 mg/40 mg for 7 days results in approximately 2.3-fold higher AUC and 2-fold higher Cmax of omeprazole at steady state compared to the first day of dosing.

The inter-subject variability of omeprazole pharmacokinetic parameters were high with % CVs ranging from 33% to 136%.

Food Effect:

Aspirin: Administration of YOSPRALA with high-fat (approximately 50%) and high-calorie (800-1000 calorie) meal in healthy subjects does not affect the extent of absorption of aspirin as measured by salicylic acid AUC and Cmax but significantly prolongs salicylic acid tmax by about 10 hours. Administration of YOSPRALA 60 minutes before a high-fat, high-calorie meal has essentially no effect on salicylic acid AUCs, Cmax and tmax.

Omeprazole: Administration of YOSPRALA with high-fat (approximately 50%) and high-calorie (800-1000 calories) meal in healthy subjects significantly reduces the extent of absorption of omeprazole resulting in 67% and 84% reductions of AUCs and Cmax respectively relative to fasting conditions. Administration of YOSPRALA 60 minutes before high-fat, high-calorie meal reduced both the omeprazole AUC and Cmax by approximately 15% relative to fasting conditions [see Dosage and Administration (2.2)].

Distribution

Aspirin: Salicylic acid is widely distributed to all tissues and fluids in the body including the central nervous system (CNS), breast milk, and fetal tissues. The highest concentrations are found in the plasma, liver, renal cortex, heart, and lungs. The protein binding of salicylate is concentration-dependent, i.e., nonlinear. At low concentrations (less than 100 mcg/mL), approximately 90% of plasma salicylate is bound to albumin while at higher concentrations (greater than 400 mcg/mL), only about 75% is bound.

Omeprazole: Protein binding is approximately 95%.

Elimination

Metabolism

Aspirin: Aspirin (acetylsalicylic acid) is rapidly hydrolyzed in the plasma to salicylic acid such that plasma levels of aspirin are essentially undetectable 1 to 2 hours after dosing with half-life of 0.35 hrs. Salicylic acid is primarily conjugated in the liver to form salicyluric acid, a phenolic glucuronide, an acyl glucuronide, and a number of minor metabolites. Salicylate metabolism is saturable and total body clearance decreases at higher serum concentrations due to the limited ability of the liver to form both salicyluric acid and phenolic glucuronide.

Omeprazole: Omeprazole is extensively metabolized by the cytochrome P450 (CYP) enzyme system. The major part of its metabolism is dependent on the polymorphically expressed CYP2C19, responsible for the formation of hydroxyomeprazole, the major metabolite in plasma. The remaining part is dependent on another specific isoform, CYP3A4, responsible for the formation of omeprazole sulphone.

Excretion

Aspirin: The elimination of salicylic acid follows zero order pharmacokinetics; (i.e., the rate of drug elimination is constant in relation to plasma concentration). Renal excretion of unchanged drug depends upon urine pH. As urinary pH rises above 6.5, the renal clearance of free salicylate increases from 5% to greater than 80%. Following therapeutic doses, approximately 10% is excreted in the urine as salicylic acid, 75% as salicyluric acid, and 10% phenolic and 5% acyl glucuronides of salicylic acid. Half-life of salicylic acid following YOSPRALA 325 mg/40 mg tablets is 2.4 hours.

Omeprazole: Following single dose oral administration of a buffered solution of omeprazole, little if any unchanged drug was excreted in urine. The majority of the dose (about 77%) was eliminated in urine as at least six metabolites. Two were identified as hydroxyomeprazole and the corresponding carboxylic acid. The remainder of the dose was recoverable in feces. This implies a significant biliary excretion of the metabolites of omeprazole. Three metabolites have been identified in plasma — the sulfide and sulfone derivatives of omeprazole, and hydroxyomeprazole. These metabolites have very little or no antisecretory activity. The half-life of the omeprazole component is 1 hour.

Specific Populations

Age: Geriatric Population

There is no specific data on the pharmacokinetics of YOSPRALA in patients over age 65.

Omeprazole: The elimination rate of omeprazole was somewhat decreased in the elderly, and bioavailability was increased. Omeprazole was 76% bioavailable when a single 40 mg oral dose of omeprazole (buffered solution) was administered to healthy elderly subjects, versus 58% in young subjects given the same dose. Nearly 70% of the dose was recovered in urine as metabolites of omeprazole and no unchanged drug was detected. The plasma clearance of omeprazole was 250 mL/min (about half that of young subjects) and its plasma half-life averaged one hour, about twice that of young healthy subjects.

Race

Pharmacokinetic differences of YOSPRALA due to race have not been studied.

Renal Impairment

The pharmacokinetics of YOSPRALA has not been determined in subjects with renal impairment.

Omeprazole: In patients with chronic renal impairment, whose creatinine clearance ranged between 10 and 62 mL/min/1.73 m^2, the disposition of omeprazole was very similar to that in healthy subjects, although there was a slight increase in bioavailability. Because urinary excretion is a primary route of excretion of omeprazole metabolites, their elimination slowed in proportion to the decreased creatinine clearance.

Hepatic Impairment

The pharmacokinetics of YOSPRALA has not been determined in subjects with hepatic impairment.

Omeprazole: In patients with chronic hepatic disease, classified as Child-Pugh Class A (n=3), B (n=4) and C (n=1), the bioavailability of omeprazole increased by approximately 100% compared to healthy subjects, reflecting decreased first-pass effect, and the plasma half-life of the drug increased to nearly 3 hours compared with the half-life in healthy subjects of 0.5 to 1 hour. Plasma clearance averaged 70 mL/min, compared with a value of 500 to 600 mL/min in healthy subjects [see Use in Specific Populations (8.7)].

Drug Interaction Studies

Effect of YOSPRALA on Other Drugs

Omeprazole is a time-dependent inhibitor of CYP2C19 and can increase the systemic exposure of co-administered drugs that are CYP2C19 substrates. In addition, administration of omeprazole increases intragastric pH and can alter the systemic exposure of certain drugs that exhibit pH-dependent solubility.

Antiretrovirals: For some antiretroviral drugs, such as rilpivirine, atazanavir and nelfinavir, decreased serum concentrations have been reported when given together with omeprazole [see Drug Interactions (7)].

Rilpivirine: Following multiple doses of rilpivirine (150 mg, daily) and omeprazole (20 mg, daily), AUC was decreased by 40%, Cmax by 40%, and Cmin by 33% for rilpivirine.

Nelfinavir: Following multiple doses of nelfinavir (1250 mg, twice daily) and omeprazole (40 mg daily), AUC was decreased by 36% and 92%, Cmax by 37% and 89% and Cmin by 39% and 75% respectively for nelfinavir and M8.

Atazanavir: Following multiple doses of atazanavir (400 mg, daily) and omeprazole (40 mg, daily, 2 hours before atazanavir), AUC was decreased by 94%, Cmax by 96%, and Cmin by 95%.

Saquinavir: Following multiple dosing of saquinavir/ritonavir (1000/100 mg) twice daily for 15 days with omeprazole 40 mg daily co-administered days 11 to 15.

AUC was increased by 82%, Cmax by 75%, and Cmin by 106%. The mechanism behind this interaction is not fully elucidated. Therefore, clinical and laboratory monitoring for saquinavir toxicity is recommended during concurrent use with omeprazole.

Clopidogrel: In a crossover clinical study, 72 healthy subjects were administered clopidogrel (300 mg loading dose followed by 75 mg per day) alone and with omeprazole (80 mg at the same time as clopidogrel) for 5 days. The exposure to the active metabolite of clopidogrel was decreased by 46% (Day 1) and 42% (Day 5) when clopidogrel and omeprazole were administered together.

Results from another crossover study in healthy subjects showed a similar pharmacokinetic interaction between clopidogrel (300 mg loading dose/75 mg daily maintenance dose) and omeprazole 80 mg daily when co-administered for 30 days. Exposure to the active metabolite of clopidogrel was reduced by 41% to 46% over this time period.

In another study, 72 healthy subjects were given the same doses of clopidogrel and 80 mg omeprazole but the drugs were administered 12 hours apart; the results were similar, indicating that administering clopidogrel and omeprazole at different times does not prevent their interaction [see Warnings and Precautions (5.4), Drug Interactions (7)].

Mycophenolate Mofetil: Administration of omeprazole 20 mg twice daily for 4 days and a single 1000 mg dose of MMF approximately one hour after the last dose of omeprazole to 12 healthy subjects in a cross-over study resulted in a 52% reduction in the Cmax and 23% reduction in the AUC of MPA [see Drug Interactions (7)].

Cilostazol: Omeprazole acts as an inhibitor of CYP2C19. Omeprazole, given in doses of 40 mg daily for one week to 20 healthy subjects in cross-over study, increased Cmax and AUC of cilostazol by 18% and 26% respectively. The Cmax and AUC of one of the active metabolites, 3,4-dihydro-cilostazol, which has 4-7 times the activity of cilostazol, were increased by 29% and 69%, respectively. Co-administration of cilostazol with omeprazole is expected to increase concentrations of cilostazol and the above mentioned active metabolite [see Drug Interactions (7)].

Diazepam: Concomitant administration of omeprazole 20 mg once daily and diazepam 0.1 mg/kg given intravenously resulted in 27% decrease in clearance and 36% increase in diazepam half-life [see Drug Interactions (7)].

Digoxin: Concomitant administration of omeprazole 20 mg once daily and digoxin in healthy subjects increased the bioavailability of digoxin by 10% (30% in two subjects) [see Drug Interactions (7)].

Effect of Other Drugs on Yosprala

Voriconazole: Concomitant administration of omeprazole and voriconazole (a combined inhibitor of CYP2C19 and CYP3A4) resulted in more than doubling of the omeprazole exposure. When voriconazole (400 mg every 12 hours for one day, followed by 200 mg once daily for 6 days) was given with omeprazole (40 mg once daily for 7 days) to healthy subjects, the steady-state Cmax and AUC0-24 of omeprazole significantly increased: an average of 2 times (90% CI: 1.8, 2.6) and 4 times (90% CI: 3.3, 4.4), respectively, as compared to when omeprazole was given without voriconazole [see Drug Interactions (7)].

12.5 Pharmacogenomics

CYP2C19, a polymorphic enzyme, is involved in the metabolism of omeprazole. The CYP2C19*1 allele is fully functional while the CYP2C19*2 and *3 alleles are nonfunctional. There are other alleles associated with no or reduced enzymatic function. Patients carrying two fully functional alleles are extensive metabolizers and those carrying two loss-of-function alleles are poor metabolizers. In extensive metabolizers, omeprazole is primarily metabolized by CYP2C19. The systemic exposure to omeprazole varies with a patient's metabolism status: poor metabolizers > intermediate metabolizers > extensive metabolizers. Approximately 3% of Caucasians and 15 to 20% of Asians are CYP2C19 poor metabolizers.

In a pharmacokinetic study of single 20 mg omeprazole dose, the AUC of omeprazole in Asian subjects was approximately four-fold of that in Caucasians [see Use in Specific Populations (8.8)].

13 NONCLINICAL TOXICOLOGY

13.1 Carcinogenesis, Mutagenesis, Impairment of Fertility

Studies to evaluate the potential effects of YOSPRALA on carcinogenicity, mutagenicity, or impairment of fertility have not been conducted.

Aspirin

Administration of aspirin for 68 weeks at 0.5% in the feed of rats was not carcinogenic.

In the Ames Salmonella assay, aspirin was not mutagenic; however, aspirin did induce chromosome aberrations in cultured human fibroblasts.

Aspirin inhibits ovulation in rats.

Omeprazole

In two 24-month carcinogenicity studies in rats, omeprazole at daily doses of 1.7, 3.4, 13.8, 44.0 and 140.8 mg/kg/day (about 0.35 to 34 times the human dose of 40 mg per day, based on body surface area) produced gastric ECL cell carcinoids in a dose-related manner in both male and female rats; the incidence of this effect was markedly higher in female rats, which had higher blood levels of omeprazole. Gastric carcinoids seldom occur in the untreated rat. In addition, ECL cell hyperplasia was present in all treated groups of both sexes. In one of these studies, female rats were treated with 13.8 mg omeprazole/kg/day (about 3.4 times the human dose of 40 mg per day, based on body surface area) for one year, then followed for an additional year without the drug. No carcinoids were seen in these rats. An increased incidence of treatment-related ECL cell hyperplasia was observed at the end of one year (94% treated vs 10% controls). By the second year the difference between treated and control rats was much smaller (46% vs 26%) but still showed more hyperplasia in the treated group. Gastric adenocarcinoma was seen in one rat (2%). No similar tumor was seen in male or female rats treated for two years. For this strain of rat no similar tumor has been noted historically, but a finding involving only one tumor is difficult to interpret. In a 52-week toxicity study in Sprague-Dawley rats, brain astrocytomas were found in a small number of males that received omeprazole at dose levels of 0.4, 2, and 16 mg/kg/day (about 0.1 to 3.2 times the human dose of 40 mg/day, based on body surface area). No astrocytomas were observed in female rats in this study. In a 2-year carcinogenicity study in Sprague-Dawley rats, no astrocytomas were found in males and females at the high dose of 140.8 mg/kg/day (about 34 times the human dose of 40 mg per day, based on body surface area). A 78-week mouse carcinogenicity study of omeprazole did not show increased tumor occurrence, but the study was not conclusive. A 26-week p53 (+/-) transgenic mouse carcinogenicity study was not positive.

Omeprazole was positive for clastogenic effects in an in vitro human lymphocyte chromosomal aberration assay, in one of two in vivo mouse micronucleus tests, and in an in vivo bone marrow cell chromosomal aberration assay. Omeprazole was negative in the in vitro Ames Salmonella typhimurium assay, an in vitro mouse lymphoma cell forward mutation assay and an in vivo rat liver DNA damage assay.

Omeprazole at oral doses up to 138 mg/kg/day (about 34 times the human dose of 40 mg per day, based on body surface area) was found to have no effect on fertility and reproductive performance.

In 24-month carcinogenicity studies in rats, a dose-related significant increase in gastric carcinoid tumors and ECL cell hyperplasia was observed in both male and female animals. Carcinoid tumors have also been observed in rats subjected to fundectomy or long-term treatment with other proton pump inhibitors or high doses of H2-receptor antagonists.

13.2 Animal Toxicology and/or Pharmacology

Aspirin

The acute oral 50% lethal dose in rats is about 1.5 g/kg and in mice 1.1 g/kg. Renal papillary necrosis and decreased urinary concentrating ability occur in rodents chronically administered high doses. Dose-dependent gastric mucosal injury occurs in rats and humans. Mammals may develop aspirin toxicosis associated with GI symptoms, circulatory effects, and central nervous system depression [see Overdosage (10)].

Omeprazole

Reproductive Toxicology Studies

Reproductive studies conducted with omeprazole in rats at oral doses up to 138 mg/kg/day (about 34 times the human dose on a body surface area basis) and in rabbits at doses up to 69 mg/kg/day (about 34 times the human dose on a body surface area basis) did not disclose any evidence for a teratogenic potential of omeprazole. In rabbits, omeprazole in a dose range of 6.9 to 69.1 mg/kg/day (about 3.4 to 34 times the human dose on a body surface area basis) produced dose-related increases in embryo-lethality, fetal resorptions, and pregnancy disruptions. In rats, dose-related embryo/fetal toxicity and postnatal developmental toxicity were observed in offspring resulting from parents treated with omeprazole at 13.8 to 138.0 mg/kg/day (about 3.4 to 34 times the human doses on a body surface area basis).

Juvenile Animal Study

A 28-day toxicity study with a 14-day recovery phase was conducted in juvenile rats with esomeprazole magnesium at oral doses of 70 to 280 mg/kg/day (about 17 to 67 times a daily oral human dose of 40 mg on a body surface area basis). An increase in the number of deaths at the high dose of 280 mg/kg/day was observed when juvenile rats were administered esomeprazole magnesium from postnatal day 7 through postnatal day 35. In addition, doses equal to or greater than 140 mg/kg/day (about 34 times a daily oral human dose of 40 mg on a body surface area basis), produced treatment-related decreases in body weight (approximately 14%) and body weight gain, decreases in femur weight and femur length, and affected overall growth. Comparable findings described above have also been observed in this study with another esomeprazole salt, esomeprazole strontium, at equimolar doses of esomeprazole.

14 CLINICAL STUDIES

Aspirin Trials

Ischemic Stroke and Transient Ischemic Attack (TIA)

In clinical trials of subjects with TIA due to fibrin platelet emboli or ischemic stroke, aspirin has been shown to significantly reduce the risk of the combined endpoint of stroke or death and the combined endpoint of TIA, stroke, or death by about 13 to18%.

Prevention of Recurrent MI and Unstable Angina Pectoris

These indications are supported by the results of six large, randomized, multi-center, placebo-controlled trials of predominantly male post-MI subjects and one randomized placebo-controlled study of men with unstable angina pectoris. Aspirin therapy in MI subjects was associated with a significant reduction (about 20%) in the risk of the combined endpoint of subsequent death and/or nonfatal reinfarction in these patients. In aspirin-treated unstable angina patients the event rate was reduced to 5% from the 10% rate in the placebo group.

Chronic Stable Angina Pectoris

In a randomized, multi-center, double-blind trial designed to assess the role of aspirin for prevention of MI in patients with chronic stable angina pectoris, aspirin significantly reduced the primary combined endpoint of nonfatal MI, fatal MI, and sudden death by 34%. The secondary endpoint for vascular events (first occurrence of MI, stroke, or vascular death) was also significantly reduced (32%).

Revascularization Procedures

Most patients who undergo coronary artery revascularization procedures have already had symptomatic coronary artery disease for which aspirin is indicated. Similarly, patients with lesions of the carotid bifurcation sufficient to require carotid endarterectomy are likely to have had a precedent event. Aspirin is recommended for patients who undergo revascularization procedures if there is a preexisting condition for which aspirin is already indicated.

YOSPRALA trials

Two randomized, multi-center, double-blind trials (Study 1 and Study 2) evaluated the omeprazole component by comparing the incidence of gastric ulcer formation in 524 patients randomized to YOSPRALA 325 mg/40 mg tablets and 525 patients randomized to EC-aspirin 325 mg. Patients were included with a cerebro- or cardiovascular diagnosis if they had been taking daily aspirin 325 mg for at least 3 months, were expected to require daily aspirin 325 mg therapy for at least 6 months and were over 55 years old. Subjects between 18 and 55 years old were also required to have a documented history of gastric or duodenal ulcer within the past 5 years. The majority of patients were male (71%) and white (90%). The majority (57%) of patients were ≥65 years of age. Approximately 11% were also on chronic NSAID therapy.

Studies 1 and 2 showed that YOSPRALA given as 325 mg/40 mg tablets once daily statistically significantly reduced the 6-month cumulative incidence of gastric ulcers compared to EC-aspirin 325 mg once daily. The results at one month, three months, and six months treatment are presented in Table 4.

Table 4: Cumulative Incidence of Gastric Ulcers at 1, 3, and 6 Months
 | Study 1 |  | Study 2
 | YOSPRALA N=265 Number (%) | EC-Aspirin N=265 Number (%) | YOSPRALA N=259 Number (%) | EC-Aspirin N=260 Number (%)
0-1 Month | 3 (1.1) | 10 (3.8) | 1 (0.4) | 8 (3.1)
0-3 Months | 8 (3.0) | 18 (6.8) | 1 (0.4) | 17 (6.5)
0-6 Months [Study 1: p=0.020 and Study 2: p=0.005 for treatment comparisons of cumulative GU incidence at 6 months.] | 10 (3.8) | 23 (8.7) | 7 (2.7) | 22 (8.5)

In both trials, patients receiving YOSPRALA 325 mg/40 mg tablets had a statistically significantly lower 6-month cumulative incidence of gastric and/or duodenal ulcers compared to EC-aspirin 325 mg (3% vs. 12%).

Upper GI bleeding was reported as a serious adverse reaction in each treatment arm; 1 gastric ulcer hemorrhage in a subject receiving YOSPRALA and 1 duodenal ulcer hemorrhage in a subject receiving EC-aspirin alone.

16 HOW SUPPLIED/STORAGE AND HANDLING

YOSPRALA (aspirin 81 mg/omeprazole 40 mg) and (aspirin 325 mg/omeprazole 40 mg) delayed-release tablets are oval, blue-green, film-coated tablets printed with 81/40 and 325/40 respectively in black ink. YOSPRALA tablets are packaged in high density polyethylene (HDPE) bottles with desiccants and are supplied as:

NDC 73568-004-30 | Bottles of 30 tablets | YOSPRALA 81/40
NDC 73568-005-02 | Bottles of 30 tablets | YOSPRALA 325/40

STORAGE AND HANDLING

Storage: Store at 25°C (77°F); excursions permitted to 15-30°C (59 to 86°F) [see USP Controlled Room Temperature]. Store in the original container with desiccant and keep the bottle tightly closed to protect from moisture. Dispense in a tight container if package is subdivided.

17 PATIENT COUNSELING INFORMATION

Advise the patient to read the FDA-approved patient labeling (Medication Guide).

Inform patients, families, or caregivers of the following before initiating therapy with YOSPRALA and periodically during the course of ongoing therapy.

Coagulation Abnormalities

Advise patients to inform their health care provider if they experience any unanticipated, prolonged or excessive bleeding or bleeding time (e.g. bruising, nose bleed) [see Warnings and Precautions (5.1)].

GI Adverse Reactions

Advise patients to stop taking YOSPRALA and call their health care provider right away if they have any of the following signs or symptoms: 1) black, bloody, or tarry stools; 2) coughing up blood or vomit that looks like coffee grounds; 3) severe nausea, vomiting, or stomach pain [see Warnings and Precautions (5.2)].

Bleeding Risk with Use of Alcohol

Advise patients to avoid heavy alcohol use (three or more drinks every day) during treatment with YOSPRALA during treatment with YOSPRALA [see Warnings and Precautions (5.3)].

Drug Interactions

Advise patients to report to their healthcare provider before starting treatment with any of the following:

- Rilpivirine-containing products [see Contraindications (4)].
- Clopidogrel, ticagrelor, St. John's Wort or rifampin; or, if they take high-dose methotrexate [see Warnings and Precautions (5.4, 5.5, 5.15, 5.17)].

Renal Failure

Advise patients to report to their health care provider if they develop kidney problems (e.g. changes in urination, swelling, skin rash/itching, ammonia breath) [see Warnings and Precautions (5.6)].

Gastric Malignancy

Advise patients to return to their healthcare provider if they have gastric symptoms while taking YOSPRALA or after completing treatment [see Warnings and Precautions (5.7)].

Acute Interstitial Nephritis

Advise patients to call their healthcare provider immediately if they experience signs and/or symptoms associated with acute interstitial nephritis [see Warnings and Precautions (5.8)].

Clostridium difficile-Associated Diarrhea

Advise patients to call their health care provider immediately if they experience diarrhea that does not improve [see Warnings and Precautions (5.9)].

Bone Fracture

Advise patients to report any fractures, especially of the hip, wrist or spine, to their health care provider [see Warnings and Precautions (5.10)].

Cutaneous and Systemic Lupus Erythematosus

Advise patients to immediately call their health care provider for any new or worsening of symptoms associated with cutaneous or systemic lupus erythematosus [see Warnings and Precautions (5.11)].

Hepatic Impairment

Advise patients to report to their health care provider if they develop liver problems (e.g. skin and eyes that appear yellowish, abdominal pain and swelling, itchy skin, dark urine color) [see Warnings and Precautions (5.12)].

Cyanocobalamin (Vitamin B-12) Deficiency

Advise patients to report any clinical symptoms that may be associated with cyanocobalamin deficiency to their health care provider if they have been receiving YOSPRALA for longer than 3 years [see Warnings and Precautions (5.13)].

Hypomagnesemia

Advise patients to report any clinical symptoms that may be associated with hypomagnesemia to their health care provider, if they have been receiving YOSPRALA for at least 3 months [see Warnings and Precautions (5.14)].

Fetal Toxicity

Inform pregnant women to avoid use of YOSPRALA and other NSAIDs starting at 30 weeks gestation because of the risk of the premature closure of the fetal ductus arteriosus [see Warnings and Precautions (5.18) and Use in Specific Populations (8.1)].

Lactation

Advise women that breastfeeding is not recommended during treatment with YOSPRALA [see Use in Specific Populations (8.2)].

Infertility

Advise females of reproductive potential that NSAIDs, including YOSPRALA, may be associated with reversible infertility [see Use in Specific Populations (8.3)].

Administration [see Dosage and Administration (2.2)]

Advise patients:

- To take YOSPRALA once daily at least 60 minutes before a meal.
- The tablets are to be swallowed whole with liquid. Do not split, chew, crush or dissolve the tablet.
- If a dose is missed, administer as soon as possible. However, if the next scheduled dose is due, do not take the missed dose, and take the next dose on time. Do not take two doses at one time to make up for a missed dose, unless advised by their health care provider.
- Not to stop taking YOSPRALA suddenly as this could increase the risk of heart attack or stroke.

Manufactured for:

PHARMACEUTICA LTD.

4050 E Cotton Center Blvd Ste 60

Phoenix, Arizona 85040

MEDICATION GUIDE
YOSPRALA™ (yo SPRA lah)
(aspirin and omeprazole)
delayed-release tablets

What is the most important information I should know about YOSPRALA?

You should take YOSPRALA exactly as prescribed, at the lowest dose possible and for the shortest time needed.

YOSPRALA may help reduce the risk of stomach ulcers from aspirin use, but you could still have bleeding and stomach or intestine ulcers, or other serious stomach or intestine problems. Talk with your doctor.

Tell your doctor if you have unexpected bleeding, if you bleed more than usual, or if your bleeding lasts longer than is normal for you, such as increased bruising or more frequent nose bleeds.

YOSPRALA contains aspirin, a nonsteroidal anti-inflammatory drug (NSAID) and omeprazole, a proton pump inhibitor (PPI) medicine. Before taking YOSPRALA, tell your doctor if you take:

- aspirin, or any prescription or over-the-counter medicines containing aspirin or other NSAIDs.
- clopidogrel bisulphate (PLAVIX®). You should not take clopidogrel bisulphate (PLAVIX®) if you take YOSPRALA.
- ticagrelor (BRILINTA®).

Do not stop taking YOSPRALA without talking with your doctor. Stopping YOSPRALA suddenly could increase your risk of having a heart attack or stroke.

YOSPRALA can cause serious side effects, including:

- A type of kidney problem (acute interstitial nephritis). Some people who take proton pump inhibitor (PPI) medicines, including YOSPRALA, may develop a kidney problem called acute interstitial nephritis that can happen at any time during treatment with YOSPRALA. Call your doctor right away if you have a decrease in the amount that you urinate or if you have blood in your urine.
- Diarrhea caused by an infection (Clostridium difficile) in your intestines. Call your doctor right away if you have watery stools or stomach pain that does not go away. You may or may not have a fever.
- Bone fractures (hip, wrist, or spine). Bone fractures in the hip, wrist, or spine may happen in people who take multiple daily doses of PPI medicines and for a long period of time (a year or longer). Tell your doctor if you have a bone fracture, especially in the hip, wrist, or spine.
- Certain types of lupus erythematosus. Lupus erythematosus is an autoimmune disorder (the body's immune cells attack other cells or organs in the body). Some people who take PPI medicines, including YOSPRALA, may develop certain types of lupus erythematosus or have worsening of the lupus they already have. Call your doctor right away if you have new or worsening joint pain or a rash on your cheeks or arms that gets worse in the sun.

Talk to your doctor about your risk of these serious side effects.

YOSPRALA can have other serious side effects. See "What are the possible side effects of YOSPRALA?"

What is YOSPRALA?

YOSPRALA is a prescription medicine used:

- in people who have had heart problems or strokes caused by blood clots, to help reduce their risk of further heart problems or strokes, and
- who are at risk of developing stomach ulcers with aspirin.

The aspirin in YOSPRALA is used:

- to help reduce the risk of strokes and death in people who have previously had certain types of "mini strokes" (transient ischemic attacks or TIAs) or strokes.
- to help reduce the risk of heart attack and death in people who have previously had a heart attack or a type of chest pain called unstable angina pectoris.
- to help reduce the risk of heart attack and sudden death in people with a type of ongoing chest pain called chronic stable angina pectoris.
- in people who have had surgery or a procedure to improve blood flow to their heart, such as coronary artery bypass grafting (CABG), or percutaneous transluminal coronary angioplasty (PTCA), and who already have another condition that is being treated with aspirin.

The omeprazole in YOSPRALA is used:

- to help decrease the risk of developing stomach ulcers due to aspirin in people who are 55 years of age or older, or who have a history of stomach ulcers.

YOSPRALA should not be used to treat sudden signs and symptoms of a heart attack or stroke. YOSPRALA should only be used as directed by your doctor to help reduce the risk of further heart problems or strokes.

It is not known if YOSPRALA is safe and effective in children.

YOSPRALA has not been shown to reduce the risk of bleeding in the stomach or intestines that is caused by aspirin.

You should not take an aspirin tablet and an omeprazole tablet together instead of taking YOSPRALA, because they will not work the same way.

Do not take YOSPRALA if you:

- are allergic to aspirin, omeprazole, any other PPI medicine, or any of the ingredients in YOSPRALA. See the end of this Medication Guide for a complete list of ingredients in YOSPRALA.
- are allergic to any nonsteroidal anti-inflammatory drug (NSAID).
- have a medical condition with severe shortness of breath, chest tightness or pain, coughing or wheezing (asthma), sneezing, runny nose or itchy nose (rhinitis), and growths inside of your nose or sinuses (nasal polyps).
- are taking a medicine that contains rilpivirine (EDURANT, COMPLERA, ODEFSEY) used to treat HIV-1 (Human Immunodeficiency Virus).

Do not give YOSPRALA to a child who has a suspected viral infection, even if they do not have a fever. There is a risk of Reye's syndrome with YOSPRALA because it contains aspirin.

Before taking YOSPRALA, tell your doctor about all of your medical conditions, including if you:

See "What is the most important information I should know about YOSPRALA?"

- have any bleeding problems.
- drink 3 or more drinks that contain alcohol every day.
- have kidney or liver problems.
- have been told that you have low magnesium levels in your blood.
- are of Asian descent and have been told that your body's ability to break down (metabolize) omeprazole is poor or if your genotype called CYP2C19 is not known.
- are pregnant or plan to become pregnant. Talk to your doctor if you are considering taking YOSPRALA during pregnancy. You should not take YOSPRALA after 29 weeks of pregnancy.
- are breastfeeding or plan to breastfeed. The aspirin and omeprazole in YOSPRALA can pass into your breast milk and may harm your baby. Breastfeeding is not recommended during treatment with YOSPRALA. Talk to your doctor about the best way to feed your baby if you take YOSPRALA.
- are a female who can become pregnant. YOSPRALA may be related to infertility in some women that is reversible when treatment with YOSPRALA is stopped.

Tell your doctor about all of the medicines you take, including prescription and over-the-counter medicines, vitamins and herbal supplements. YOSPRALA and some other medicines can interact with each other and cause serious side effects. Do not start taking any new medicine without talking to your doctor first.

Especially tell your doctor if you take:

- clopidogrel bisulphate (PLAVIX®)
- ticagrelor (BRILINTA®)
- St. John's Wort (Hypericum perforatum)
- rifampin (Rimactane, RIFATER®, RIFAMATE® RIFADIN®)
- methotrexate (Otrexup, Rasuvo, Trexall, XATMEP)
- digoxin (LANOXIN)
- a water pill (diuretic)

How should I take YOSPRALA?

- Take YOSPRALA exactly as prescribed by your doctor.
- Take 1 YOSPRALA tablet 1 time each day.
- Take YOSPRALA at least 1 hour before a meal.
- Swallow YOSPRALA tablets whole with liquid. Do not split, chew, crush, or dissolve YOSPRALA.
- If you miss a dose of YOSPRALA, take it as soon as you remember. If it is almost time for your next dose, do not take the missed dose. Take the next dose at your regular time. Do not take 2 doses at the same time unless your doctor tells you to.
- If you take too much YOSPRALA, call your doctor or your poison control center at 1-800-222-1222 right away or go to the nearest emergency room.

What should I avoid while taking YOSPRALA?

Avoid heavy alcohol use during treatment with YOSPRALA. People who drink three or more drinks that contain alcohol every day have a higher risk of bleeding during treatment with YOSPRALA because it contains aspirin.

What are the possible side effects of YOSPRALA?

YOSPRALA can cause serious side effects, including:

See "What is the most important information I should know about YOSPRALA?"

- Stomach and intestine problems. Stop taking YOSPRALA and call your doctor right away if you have symptoms of stomach and intestine problems, including black, bloody, or tarry stools, coughing up blood or vomit that looks like coffee grounds, or severe nausea, vomiting, or stomach pain.
- Kidney failure. Long-lasting (chronic) kidney failure can happen with regular use of aspirin, a medicine in YOSPRALA. This is more likely to happen in people who already have kidney problems before treatment with YOSPRALA. Tell your doctor if you have symptoms of kidney failure, including changes in urination, swelling of the hands, ankles or feet, skin rash or itching, or your breath smells like ammonia.
- Liver problems. Long-term use of YOSPRALA at certain doses may cause liver problems. Tell your doctor if you have symptoms of liver problems, including yellowing of your skin or your eyes, stomach-area (abdominal) pain and swelling, itchy skin, and dark (tea-colored) urine.
- Low vitamin B-12 levels. Low vitamin B-12 levels in your body can happen in people who have taken YOSPRALA for a long time (more than 3 years). Tell your doctor if you have symptoms of low vitamin B-12 levels, including shortness of breath, lightheadedness, irregular heartbeat, muscle weakness, pale skin, feeling tired, mood changes, and tingling or numbness in the arms or legs.
- Low magnesium levels. Low magnesium levels in your body can happen in people who have taken YOSPRALA for at least 3 months. Tell your doctor if you have symptoms of low magnesium levels, including seizures, dizziness, irregular heartbeat, jitteriness, muscle aches or weakness, and spasms of hands, feet or voice.
- Stomach growths (fundic gland polyps). People who take PPI medicines for a long time have an increased risk of developing a certain type of stomach growths called fundic gland polyps, especially after taking PPI medicines for more than 1 year.

The most common side effects of YOSPRALA include: indigestion or heartburn and stomach-area pain, nausea, diarrhea, and chest pain behind the breastbone, for example, with eating.

These are not all the possible side effects of YOSPRALA. Call your doctor for medical advice about side effects. You may report side effects to FDA at 1-800-FDA-1088.

How should I store YOSPRALA?

- Store YOSPRALA at room temperature between 68°F to 77°F (20°C to 25°C).
- Store YOSPRALA in the original container.
- Keep the container of YOSPRALA tightly closed to protect from moisture.
- The YOSPRALA container may contain a desiccant packet to help keep your medicine dry (protect it from moisture). Keep the desiccant packet in the container. Do not throw away the desiccant packet.

Keep YOSPRALA and all medicines out of the reach of children.

General information about the safe and effective use of YOSPRALA

Medicines are sometimes prescribed for purposes other than those listed in a Medication Guide. Do not use YOSPRALA for a condition for which it was not prescribed. Do not give YOSPRALA to other people, even if they have the same symptoms that you have. It may harm them. You can ask your doctor or pharmacist for information about YOSPRALA that is written for health professionals.

What are the ingredients in YOSPRALA?

Active ingredients: aspirin and omeprazole

Inactive ingredients: carnauba wax, colloidal silicon dioxide, corn starch, FD&C Blue #2, glyceryl monostearate, hydroxypropyl methycellulose, methacrylic acid copolymer dispersion, microcrystalline cellulose, polydextrose, polyethylene glycol, polysorbate 80, povidone, pre-gelatinized starch, sodium phosphate dibasic anhydrous, stearic acid, talc, titanium dioxide, triacetin, triethyl citrate, yellow iron oxide.

Manufactured for: PHARMACEUTICA LTD.4050 E Cotton Center Blvd Ste 60 Phoenix, Arizona 85040

This Medication Guide has been approved by the U.S. Food and Drug Administration.

Revised: September 2018 r1

70037927

PRINCIPAL DISPLAY PANEL - 81 mg/40 mg Tablet Bottle Label

NDC 73568-004-30

30 tablets

Yosprala®

(aspirin and omeprazole)

delayed-release tablets

81 mg/40 mg tablets

Dispense with accompanying Medication Guide

Do not split, chew, crush, or dissolve the tablet.

PHARMACEUTICA LTD

Rx only

PRINCIPAL DISPLAY PANEL - 325 mg/40 mg Tablet Bottle Label

NDC 73568-005-02

30 tablets

Yosprala®

(aspirin and omeprazole)

delayed-release tablets

325 mg/40 mg tablets

Dispense with accompanying Medication Guide

Do not split, chew, crush, or dissolve the tablet.

PHARMACEUTICA LTD

Rx only